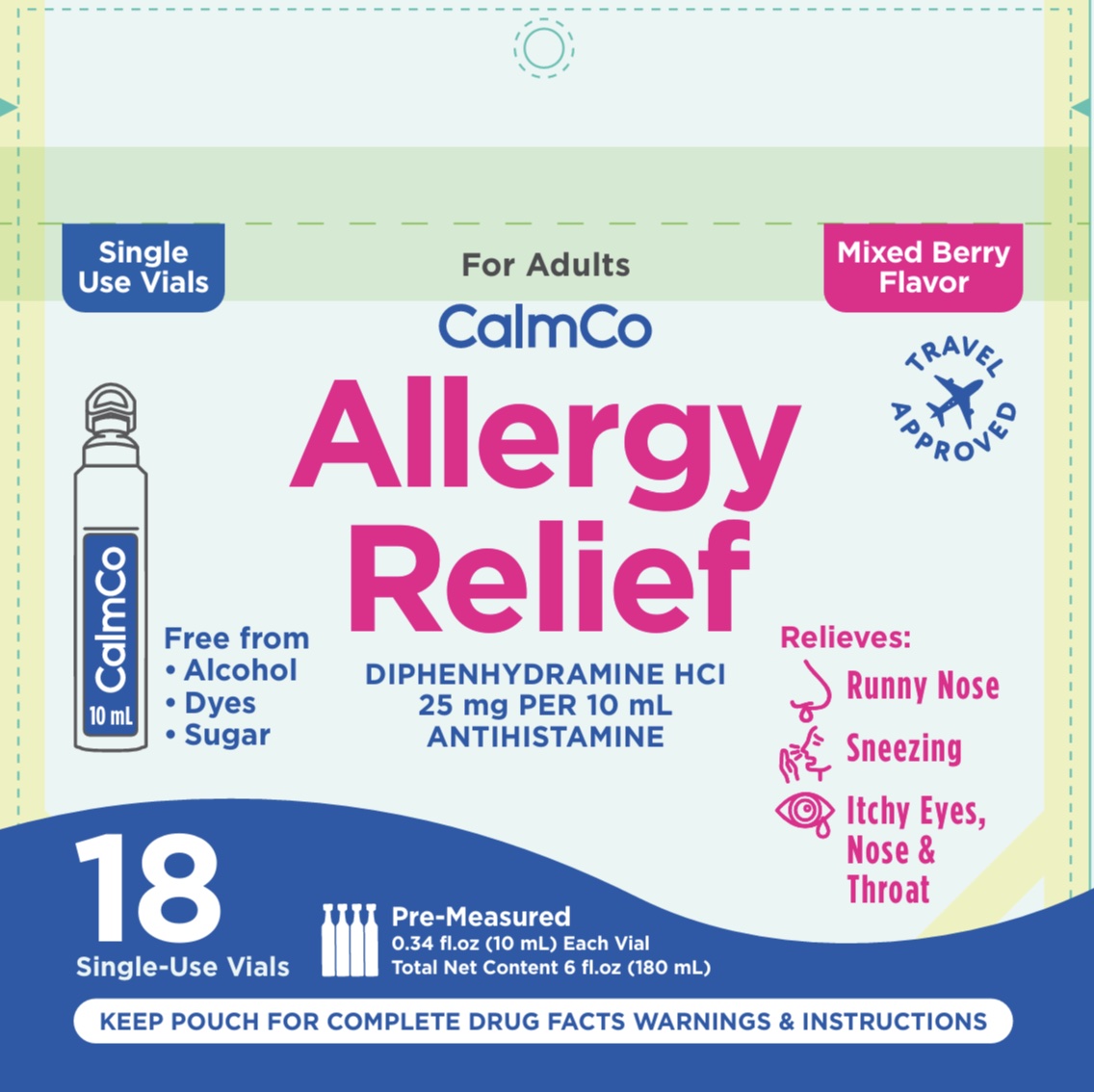 DRUG LABEL: Calmco
NDC: 73282-2524 | Form: SOLUTION
Manufacturer: CalmCo LLC
Category: otc | Type: HUMAN OTC DRUG LABEL
Date: 20251230

ACTIVE INGREDIENTS: DIPHENHYDRAMINE HYDROCHLORIDE 25 mg/5 mL
INACTIVE INGREDIENTS: SUCRALOSE; ANHYDROUS CITRIC ACID; SORBITOL; SODIUM BENZOATE; GLYCERIN; WATER; PROPYLENE GLYCOL; XYLITOL; CARBOXYMETHYLCELLULOSE

Calmco Adult Allergy Relief (CC)

Drug Facts

.

Active ingredient and Purpose

Active ingredient (in each 10 mL vial) | Purpose
Diphenhydramine HCl 25 mg............... | Antihistamine

Uses

Temporarily relieves

- runny nose
- sneezing
- itchy nose or throat
- itchy, watery eyes due to hay fever
- other upper respiratory allergies

Warnings

.

Do not use

- with any other product containing diphenhydramine, even one used on skin

Ask a doctor before use if you

- have a breathing problem such as emphysema or chronic bronchitis
- have glaucoma
- have trouble urinating due to an enlarged prostate gland
- are taking sedatives or tranquilizers

When using this product

- avoid consuming alcohol beverages
- may cause marked drowsiness
- alcohol, sedatives, and tranquilizers may increase the drowsiness effect
- use caution when driving a motor vehicle or operating machinery
- excitability may occur, especially in children

If pregnant or breastfeeding,

ask a healthcare professional before use.

KEEP OUT OF REACH OF CHILDREN.

In case of accidental overdose, get medical help or contact a Poison Control Center right away (1-800-222-1222).

Directions

- do not exceed 12 vials in a 24-hour period
- follow the “Easy to Use” instructions on pouch

Age | Dose
Adults and children 12 years of age and older | take 1 - 2 vials every 4-6 hours
children under 12 years of age | do not use

Other information

- each 10 mL vial contains: sodium 4mg
- store between 68-77°F (20-25°C)
- do not use if pouch has been torn open or vial is punctured or open

Inactive ingredients

Anhydrous citric acid, carboxymethylcellulose, flavors, glycerin, propylene glycol, sodium benzoate, sorbitol solution, sucralose, water, xylitol

Questions or comments?

+1 941-203-4590 (M-F) 9am-5pm EST or visit www.calmco.com

Distributed by: CalmCo LLC, Sarasota, FL 34240

Made in Dominican Republic